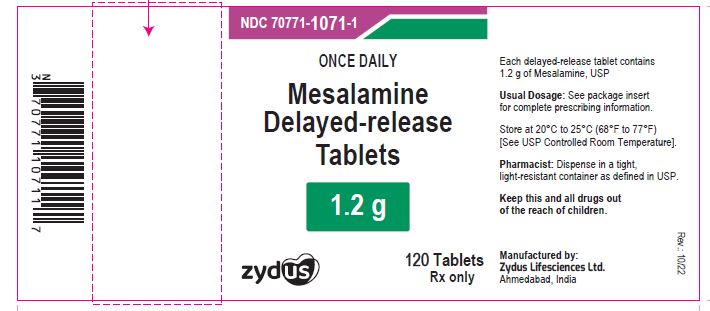 DRUG LABEL: mesalamine
NDC: 70771-1071 | Form: TABLET, DELAYED RELEASE
Manufacturer: Zydus Lifesciences Limited
Category: prescription | Type: HUMAN PRESCRIPTION DRUG LABEL
Date: 20241130

ACTIVE INGREDIENTS: MESALAMINE 1.2 g/1 1
INACTIVE INGREDIENTS: CARBOXYMETHYLCELLULOSE SODIUM; CELLULOSE, MICROCRYSTALLINE; FERRIC OXIDE RED; FERRIC OXIDE YELLOW; HYPROMELLOSES; MAGNESIUM STEARATE; METHACRYLIC ACID; POLYETHYLENE GLYCOL, UNSPECIFIED; SILICON DIOXIDE; SODIUM STARCH GLYCOLATE TYPE A POTATO; TALC; TITANIUM DIOXIDE; TRIETHYL CITRATE

MESALAMINE DELAYED-RELEASE TABLETS

PACKAGE LABEL.PRINCIPAL DISPLAY PANEL

NDC 70771-1071-1

Mesalamine Delayed-release Tablets, 1.2 g

Rx only

120 tablets